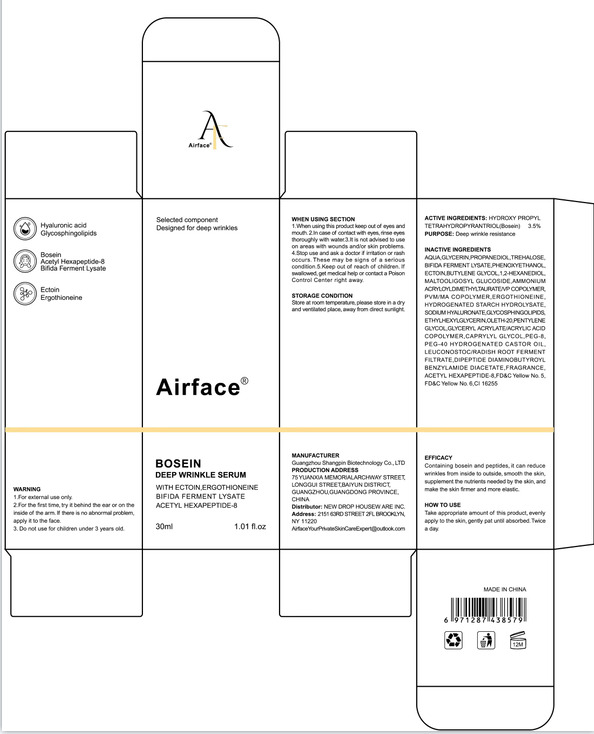 DRUG LABEL: Airface  BosEin deep wrinkle serum
NDC: 84581-001 | Form: LIQUID
Manufacturer: GUANGZHOU SHANGPIN BIOTECHNOLOGY CO.,LTD
Category: otc | Type: HUMAN OTC DRUG LABEL
Date: 20240725

ACTIVE INGREDIENTS: HYDROXYPROPYL TETRAHYDROPYRANTRIOL 3.5 g/100 mL
INACTIVE INGREDIENTS: GLYCERYL ACRYLATE/ACRYLIC ACID COPOLYMER (300000 CP AT 2%); CAPRYLYL GLYCOL; FD&C YELLOW NO. 5; FD&C YELLOW NO. 6; METHYL VINYL ETHER AND MALEIC ANHYDRIDE COPOLYMER (1100000 WAMW); HYDROGENATED STARCH HYDROLYSATE; FRAGRANCE FRESH CITRUS FLORAL ORC1501495; WATER; GLYCERIN; PROPANEDIOL; TREHALOSE; PHENOXYETHANOL; ECTOINE; MALTOOLIGOSYL GLUCOSIDE; BUTYLENE GLYCOL; ETHYLHEXYLGLYCERIN; ERGOTHIONEINE; HYALURONATE SODIUM; OLETH-20; LEUCONOSTOC/RADISH ROOT FERMENT FILTRATE; POLYETHYLENE GLYCOL 400; AMMONIUM ACRYLOYLDIMETHYLTAURATE/VP COPOLYMER; POLYOXYL 40 HYDROGENATED CASTOR OIL; 1,2-HEXANEDIOL; DIPEPTIDE DIAMINOBUTYROYL BENZYLAMIDE DIACETATE; ACETYL HEXAPEPTIDE-8; PONCEAU 4R; PENTYLENE GLYCOL

84581-001

Active Ingredient(s)

HYDROXYPROPYL TETRAHYDROPYRANTRIOL 3.5%

Purpose

Deep wrinkle resistance

Use

Take appropriate amount of this product, evenly apply to the skin, gently pat until absorbed. Twice a day.

Warnings

1.For external use only.
2.For the first time, try it behind the ear or on the inside of the arm. If there is no abnormal problem, apply it to the face.
3. Do not use for children under 3 years old.

Do not use

Donnotuse on da maged skin(cuts, abrasionseczema, sunburn)f you are allergic to any of the ingredients in this product.

WHEN USING

1.When using this product keep out of eyes and mouth.

2.In case of contact with eyes, rinse eyes thoroughly with water.

3.It is not advised to use on areas with wounds and/or skin problems.

4.Stop use and ask a doctor if rritation or rash occurs.'These may be signs of a serious condition.

5.Keep out of reach of children. If swallowed, get medical help or contact a Poison Control Center right away.

Stop use and ask a doctor if irritation or rash occurs.

KEEP OUT OF REACH OF CHILDREN

If swallowed, get medical help or contact a Poison Control Center right away.

Directions

Take appropriate amount of this product, evenly apply to the skin, gently pat until absorbed. Twice a day.

Other information

Store at room temperature, please store ina dry and ventilated place, away from direct sunlight.

Inactive ingredients

AQUA,GLYCERIN,PROPANEDIOL,TREHALOSE, BIFIDA FERMENT LYSATE ,PHENOXYETHANOL,
ECTOIN,BUTYLENE GLYCOL,1,2-HEXANEDIOL, MALTOOLIGOSYL GLUCOSIDE ,AMMONIUM
ACRYLOYLDIMETHYLTAURATENP COPOLYMER, PVM/MA COPOLYMER,ERGOTHIONEINE,
HYDROGENATED STARCH HYDROLYSATE, SODIUM HYALURONATE,GLYCOSPHINGOLIPIDS,
ETHYLHEXYLGLYCERIN,OLETH-20,PENTYLENE GLYCOL,GLYCERYL ACRYLATE/ACRYLIC ACID
COPOLYMER,CAPRYLYL GLYCOL,PEG-8, PEG-40 HYDROGENATED CASTOR OIL,
LEUCONOSTOC/RADISH ROOT FERMENT FILTRATE,DIPEPTIDE DIAMINOBUTYROYL
BENZYLAMIDE DIACETATE, FRAGRANCE, ACETYL HEXAPEPTIDE-8.FD&C Yellow No. 5,
FD&C Yellow No.6,CI 16255